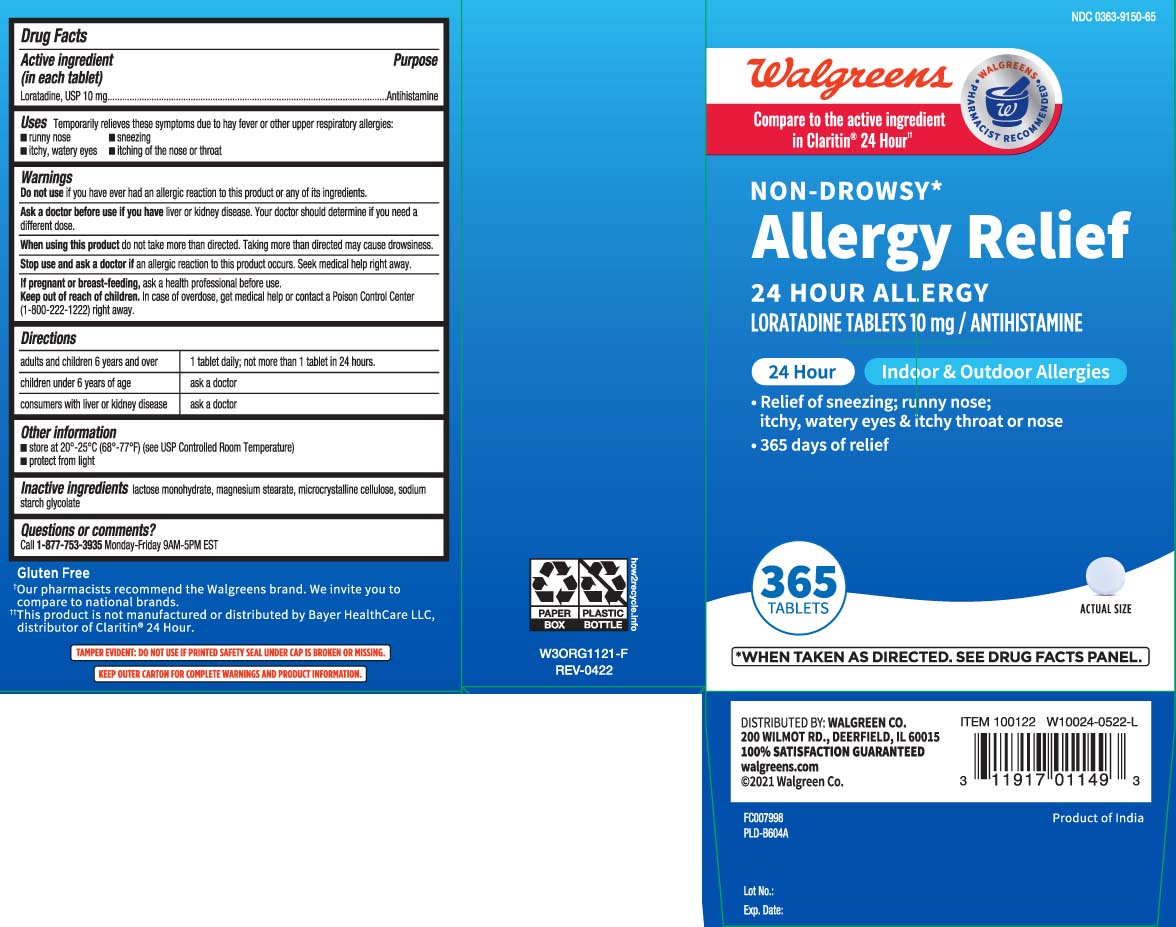 DRUG LABEL: Wal-itin
NDC: 0363-9150 | Form: TABLET
Manufacturer: Walgreens
Category: otc | Type: HUMAN OTC DRUG LABEL
Date: 20250828

ACTIVE INGREDIENTS: LORATADINE 10 mg/1 1
INACTIVE INGREDIENTS: LACTOSE MONOHYDRATE; MAGNESIUM STEARATE; MICROCRYSTALLINE CELLULOSE; SODIUM STARCH GLYCOLATE TYPE A CORN

Drug Facts

Active ingredient (in each tablet)

Loratadine, USP 10 mg

Purpose

Antihistamine

Uses

temporarily relieves these symptoms due to hay fever or other upper respiratory allergies:

- runny nose
- sneezing
- itchy, watery eyes
- itching of the nose or throat

Warnings

Do not use

if you have ever had an allergic reaction to this product or any of its ingredients.

Ask a doctor before use if you have

liver or kidney disease. Your doctor should determine if you need a different dose.

When using this product

do not take more than directed. Taking more than directed may cause drowsiness.

Stop use and ask a doctor if

an allergic reaction to this product occurs. Seek medical help right away.

If pregnant or breast-feeding,

ask a health professional before use.

Keep out of reach of children.

In case of overdose, get medical help or contact a Poison Control Center (1-800-222-1222) right away.

Directions

adults and children 6 years and over | 1 tablet daily; not more than 1 tablet in 24 hours
children under 6 years of age | ask a doctor
consumers with liver or kidney disease | ask a doctor

Other information

- store between 20º-25ºC (68º-77ºF) (see UPS Controlled Room Temperature)
- protect from light

Inactive ingredients

lactose monohydrate, magnesium stearate, microcrystalline cellulose, sodium starch glycolate

Questions or comments?

Call 1-877-753-3935 Monday-Friday 9AM-5PM EST

Principal Display Panel

Compare to the active ingredient in Claritin® 24 Hour††

NON-DROWSY*

Allergy Relief

24 HOUR ALLERGY

LORATADINE TABLETS, 10 mg / ANTIHISTAMINE

24 HOUR Indoor & Outdoor Allergies

- Relief of sneezing; runny nose; itchy, watery eyes & Itchy throat or nose
- 365 days of relief

*WHEN TAKEN AS DIRECTED. SEE DRUG FACTS PANEL.

TABLETS

Gluten Free

†This product is not manufactured or distributed by Bayer Healthcare LLC, distributor of Claritin® 24 Hour.

TAMPER EVIDENT: DO NOT USE IF PRINTED SAFETY SEAL UNDER CAP IS BROKEN OR MISSING.

KEEP OUTER CARTON FOR COMPLETE WARNINGS AND PRODUCT INFORMATION.

DISTRIBUTED BY: WALGREEN CO.

200 WILMOT RD., DEERFIELD, IL 60015

walgreens.com

Package Label

WALGREENS Non-Drowsy Allergy Relief